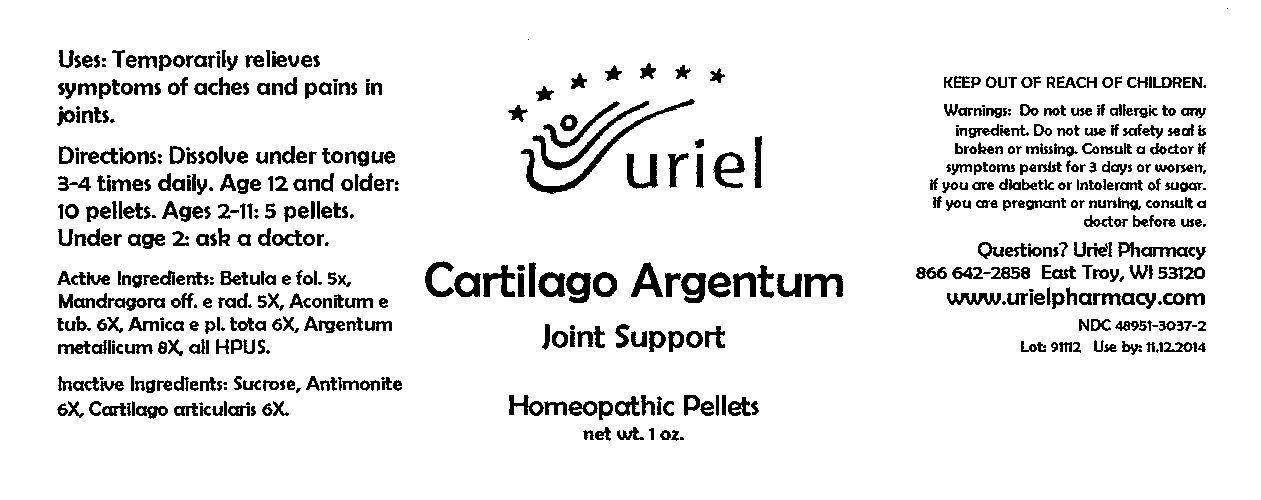 DRUG LABEL: Cartilago Argentum Joint Support
NDC: 48951-3037 | Form: PELLET
Manufacturer: Uriel Pharmacy Inc
Category: homeopathic | Type: HUMAN OTC DRUG LABEL
Date: 20091231

ACTIVE INGREDIENTS: MANDRAGORA OFFICINARUM ROOT 5 [hp_X]/1 1; BETULA PENDULA LEAF 5 [hp_X]/1 1; ACONITUM NAPELLUS ROOT 6 [hp_X]/1 1; ARNICA MONTANA 6 [hp_X]/1 1; SILVER 8 [hp_X]/1 1
INACTIVE INGREDIENTS: SUCROSE

Cartilago Argentum Joint Support Pellets - 1 oz.

Purpose

Uses: Temporarily relieves symptoms of aches and pains in joints.

Dosage & Administration

Directions: Dissolve under tongue 3-4 times daily. Age 12 and older: 10 pellets. Ages 2-11: 5 pellets. Under age 2: ask a doctor.

OTC-Active Ingredient

Active Ingredients: Betula e fol. 5x, Mandragora off. e rad. 5X, Aconitum e tub. 6X, Arnica e pl. tota 6X, Argentum metallicum 8X, all HPUS.

Inactive Ingredient

Inactive Ingredients: Sucrose, Antimonite 6X, Cartilago articularis 6X.

Keep out of reach of children

Do not use section

Warnings:Do not use if allergic to any ingredient. Do not use if safety seal is broken or missing.

Ask doctor section

Consult a doctor if symptoms are serious or persist for 3 days, if you are diabetic or intolerant of sugar.

Pregnancy or breast feeding section

If you are pregnant or nursing, consult a doctor before use.

Questions section

Questions? Uriel Pharmacy

866 642-2858 East Troy, WI 53120

www.urielpharmacy.com

NDC 48951-3037-2

Principal Display Panel

Cartilago Argentum

Joint Support

Homeopathic Pellets

net wt. 1 oz.